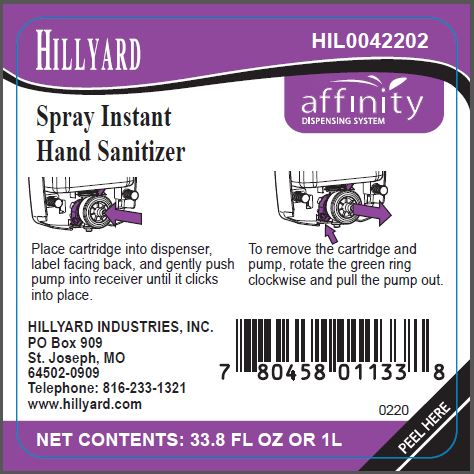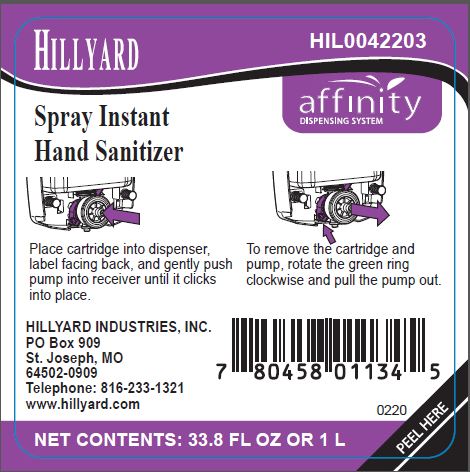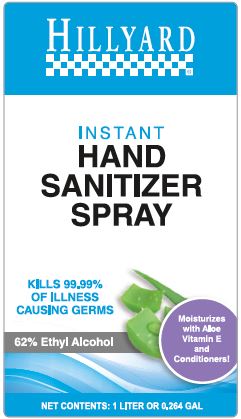 DRUG LABEL: Instant Hand Sanitizer
NDC: 76402-422 | Form: SPRAY
Manufacturer: Hillyard GMP
Category: otc | Type: HUMAN OTC DRUG LABEL
Date: 20241231

ACTIVE INGREDIENTS: ALCOHOL 62 mL/100 mL
INACTIVE INGREDIENTS: WATER; PEG-10 DIMETHICONE (600 CST); GLYCERIN; CITRIC ACID MONOHYDRATE; .ALPHA.-TOCOPHEROL; ALOE VERA LEAF

Spray Instant Hand Sanitizer

Active Ingredients

Ethyl Alcohol 62.0%

Purpose

Antimicrobial

Uses

- For hand sanitizing to decrease bacteria on the skin.
- Recommended for repeated use.

Warnings

- For External Use Only

Flammable. Keep away from fire or flame.

When using this product

avoid contact with eyes. In case of eye contact, flush eyes thoroughly with water.

Stop use and ask a doctor if

irritation or redness develops, or if condition persists for more than 72 hours.

Keep out of reach of children.

If swallowed, get medical help or contact a Poison Control Center right away.

Directions

- Pump enough spray into palm of hand to cover both hands.
- Rub thoroughly over all surfaces of both hands.
- Rub hands together briskly until dry.
- Children under 6 years of age should be supervised when using this product.

Inactive Ingredients

Water, PEG-10 Dimethicone, Glycerin, Fragrance, Citric Acid, Vitamin E, Aloe Barbadensis Leaf Juice.

Principal Display Panel – 1 Liter (Automatic Dispenser) Label

Hillyard
Spray Instant Hand Sanitizer

HIL0042202

affinity
DISPENSING SYSTEM

Place cartridge into dispenser, label facing back, and gently push pump into receiver until it clicks into place.

To remove the cartridge and pump, rotate the green ring clockwise and pull the pump out.

HILLYARD INDUSTRIES, INC.
PO Box 909
St. Joseph, MO
64502-0909
Telephone: 816-233-1321
www.hillyard.com

NET CONTENTS: 33.8 FL OZ OR 1L

PEEL HERE

Principal Display Panel – 1.00 Liter (Manual Dispenser) Label

Hillyard
Spray Instant Hand Sanitizer

HIL0042203

affinity
DISPENSING SYSTEM

Place cartridge into dispenser, label facing back, and gently push pump into receiver until it clicks into place.

To remove the cartridge and pump, rotate the green ring clockwise and pull the pump out.

HILLYARD INDUSTRIES, INC.
PO Box 909
St. Joseph, MO
64502-0909
Telephone: 816-233-1321
www.hillyard.com

NET CONTENTS: 33.8 FL OZ OR 1L

PEEL HERE

Principal Display Panel – 1.00 Liter (Manual Dispensing Pump) Label

Hillyard

INSTANT HAND SANITIZER SPRAY

KILLS 99.99% OF ILLNESS CAUSING GERMS

Moisturizes with Aloe Vitamin E and Conditioners!

62% Ethyl Alcohol

NET CONTENTS: 1 LITER OR 0.264 GAL

HILLYARD INDUSTRIES, INC.
PO Box 909
St. Joseph, MO
64502-0909
Telephone: 800-365-1555
www.hillyard.com